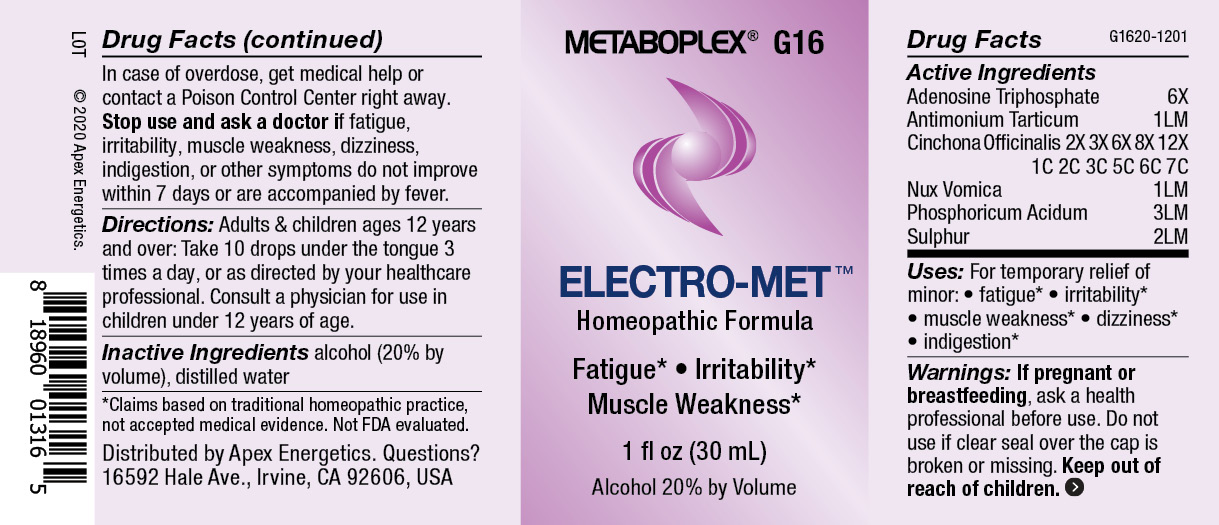 DRUG LABEL: G16
NDC: 63479-0716 | Form: SOLUTION/ DROPS
Manufacturer: Apex Energetics Inc.
Category: homeopathic | Type: HUMAN OTC DRUG LABEL
Date: 20240108

ACTIVE INGREDIENTS: PHOSPHORIC ACID 3 [hp_C]/1 mL; STRYCHNOS NUX-VOMICA SEED 1 [hp_Q]/1 mL; ANTIMONY POTASSIUM TARTRATE 1 [hp_Q]/1 mL; CINCHONA OFFICINALIS BARK 7 [hp_C]/1 mL; SULFUR 2 [hp_Q]/1 mL; ADENOSINE TRIPHOSPHATE 6 [hp_X]/1 mL
INACTIVE INGREDIENTS: WATER; ALCOHOL

G16

Active Ingredients
Adenosine Triphosphate | 6X
Antimonium Tartaricum | 1LM
Cinchona Officinalis | 2X 3X 6X 8X 12X 1C 2C 3C 5C 6C 7C
Nux Vomica | 1LM
Phosphoricum Acidum | 3LM
Sulphur | 2LM

INDICATIONS AND USAGE

Uses:

For temporary relief of minor:

fatigue*

irritability*

muscle weakness*

dizziness*

indigestion*

*Claims based on traditional homeopathic practice, not accepted medical evidence. Not FDA evaluated.

Warnings:

PURPOSE

If pregnant or breastfeeding, ask a health professional before use.

Do not use if clear seal over the cap is broken or missing.

Keep out of reach of children. In case of overdose, get medical help or contact a Poison Control Center right away.

Stop use and ask a doctor if fatigue, irritability, muscle weakness, dizziness, indigestion, or other symptoms do not improve within 7 days or are accompanied by fever.

Directions:

Adults & children ages 12 years and over: Take 10 drops under the tongue 3 times a day, or as directed by your healthcare professional. Consult a physician for use in children under 12 years of age.

Inactive Ingredients

alcohol (20% by volume), distilled water

Distributed by Apex Energetics. Questions?

16592 Hale Ave., Irvine, CA 92606, USA

PACKAGE LABEL

METABOPLEX® G16

ELECTRO-MET™

Homeopathic Formula

Fatigue*

Irritability*

Muscle Weakness*

1 fl oz (30 mL)

Alcohol 20% by Volume